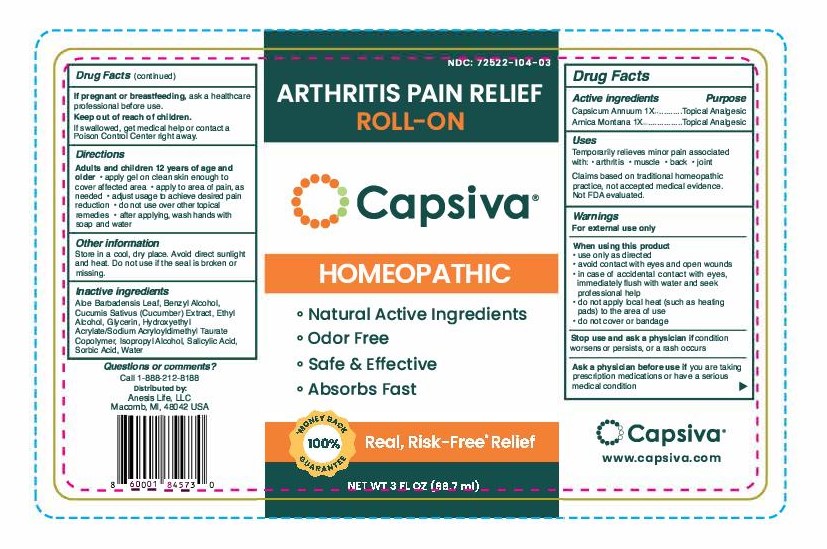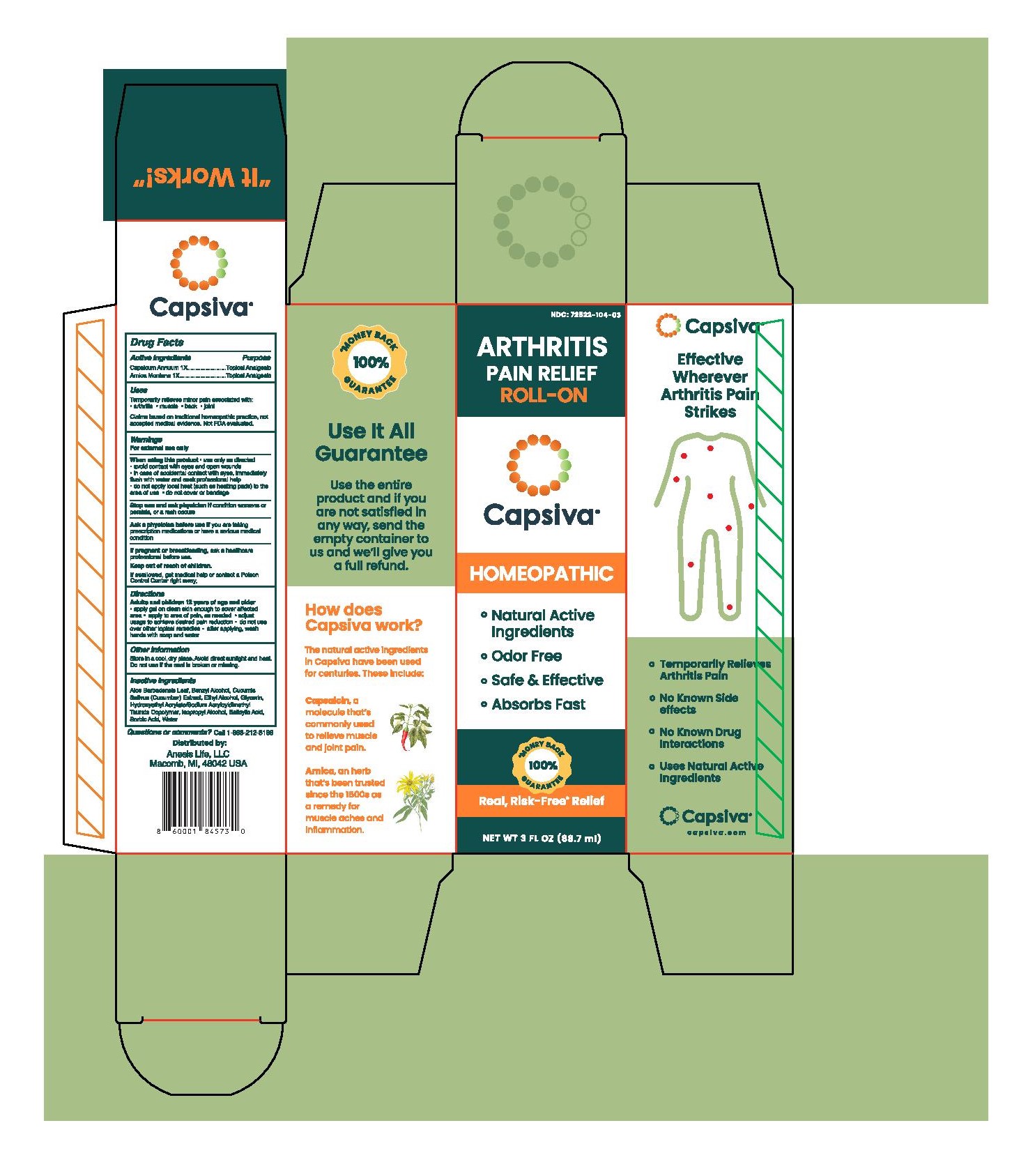 DRUG LABEL: Capsiva
NDC: 72522-104 | Form: GEL
Manufacturer: ANESIS LIFE, LLC
Category: homeopathic | Type: HUMAN OTC DRUG LABEL
Date: 20231027

ACTIVE INGREDIENTS: CAPSICUM 1 [hp_X]/88.7 mL; ARNICA MONTANA 1 [hp_X]/88.7 mL
INACTIVE INGREDIENTS: WATER; ISOPROPYL ALCOHOL; SALICYLIC ACID; CUCUMBER; ALCOHOL; BENZYL ALCOHOL; GLYCERIN; HYDROXYETHYL ACRYLATE/SODIUM ACRYLOYLDIMETHYL TAURATE COPOLYMER (45000 MPA.S AT 1%); SORBIC ACID; ALOE VERA LEAF

Capsiva 3oz Roll-On

Active ingredients

Capsicum Annuum 1X

Arnica Montana 1X

Purpose

Capsicum Annuum 1X......................Topical Analgesic

Arnica Montana 1X...........................Topical Analgesic

Uses

Temporarily relieves minor pain associated with:

- arthritis
- muscle
- back
- joint

Claims based on traditional homeopathic practices, not accepted medical evidence. Not FDA evaluated.

Warnings

For external use only

When using this product

- use only as directed
- avoid contact with eyes and open wounds
- in case of accidental contact with eyes, immediately flush with water and seek professional help
- do not apply local heat (such as heating pads) to the area of use
- do not cover or bandage

Stop use and ask physician ifcondition worsens or persists, or a rash occurs

ASK DOCTOR

Ask a physician before use ifyou are taking prescription medications or have a serious medical condition

PREGNANCY OR BREAST FEEDING

If pregnant or breastfeeding,ask a healthcare professional before use.

Keep out of reach of children. If swallowed, get medical help or contact a Poison Control Center right away.

Directions

Adults and children 12 years of age and older

- apply gel on clean skin enough to cover affected area
- apply to area of pain, as needed
- adjust usage to achieve desired pain reduction
- do not use over other topical remedies
- after applying, wash hands with soap and water

Other information

Store in a cool, dry place. Avoid direct sunlight and heat. Do not use if the seal is broken or missing.

Inactive ingredients

Aloe Barbadensis Leaf, Benzyl Alcohol, Cucumis Sativus (Cucumber) Extract, Ethyl Alcohol, Glycerin, Hydroxyethyl Acrylate/Sodium Acryloyldimethyl Taurate Copolymer, Isopropyl Alcohol, Salicylic Acid, Sorbic Acid, Water

PACKAGE LABEL

NDC: 72522-104-03

Arthritis Pain Relief Roll-On

Capsiva

Homeopathic

Natural Active Ingredients

Odor Free

Safe & Effective

Absorbs Fast

*100% Money Back Guarantee

Real, Risk-Free* Relief

Net Wt 3 oz (88.7 mL)